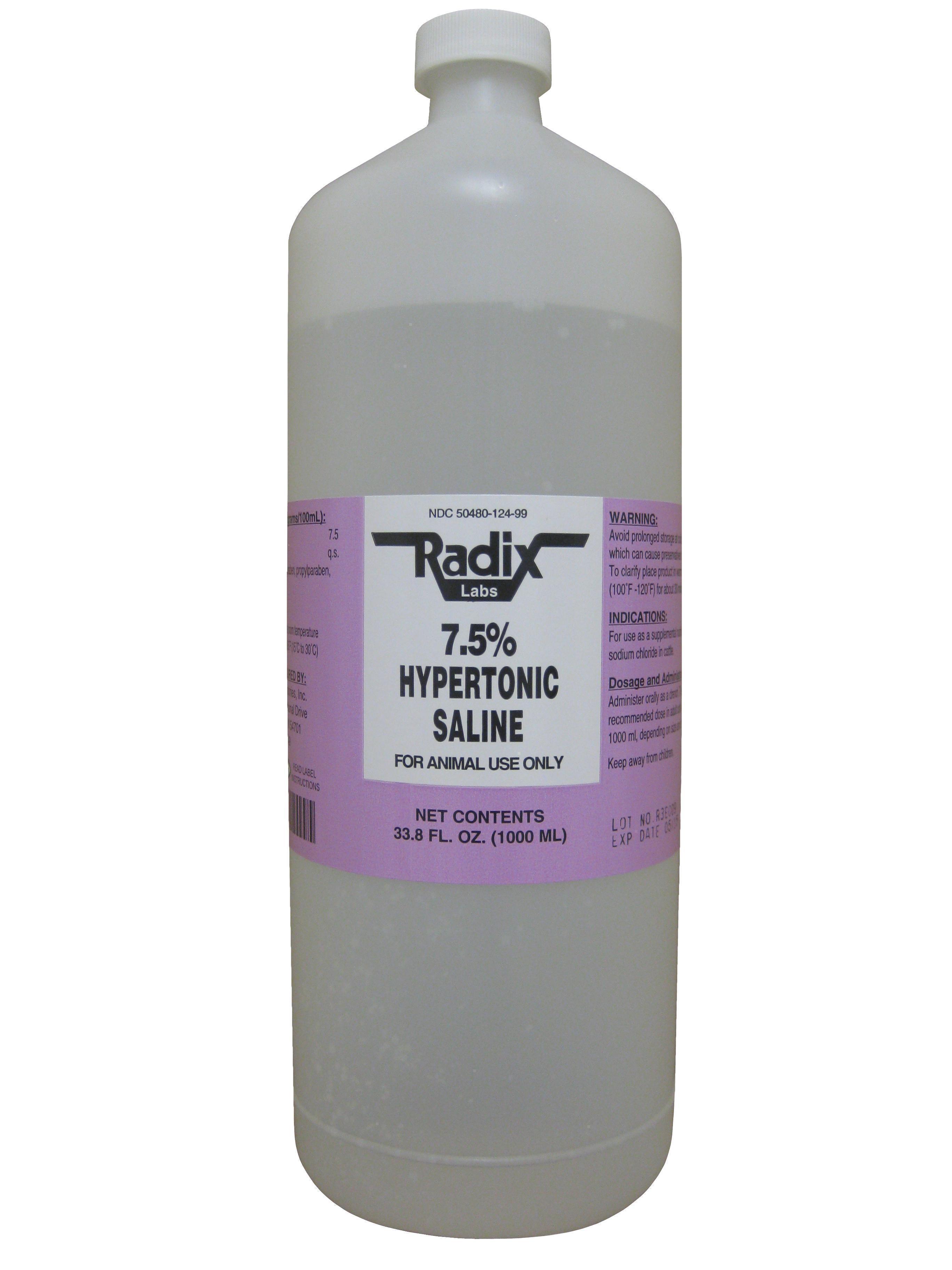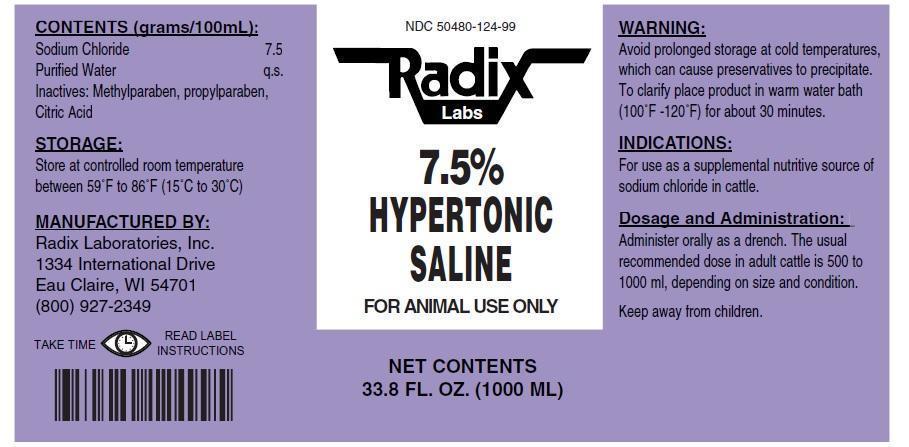 DRUG LABEL: 7.5% Hypertonic Saline
NDC: 50480-124 | Form: LIQUID
Manufacturer: Radix Laboratories, Inc.
Category: animal | Type: OTC ANIMAL DRUG LABEL
Date: 20141222

ACTIVE INGREDIENTS: SODIUM CHLORIDE 7.5 g/100 mL

7.5% Hypertonic Saline

• CONTENTS (grams/100ml):

- Sodium Chloride .....7.5

Inactives:

- Purified Water q.s.
- Methylparaben
- Propylparaben
- Citric Acid

Indications:

- For use as a supplemental nutritive source of sodium chloride in cattle.

Storage:

- Store at controlled room temperature between 59oF to 86oF (15oC -30oC).

Warnings:

- Avoid storage at cold temperatures which can cause product to become cloudy.
- To clarify place product in warm water bath (100oF-120oF) for about 30 minutes.

Dosage and administration:

- Administer orally as a drench or by use of a stomach tube.
- The usual recommended dose in adult cattle is 16.9 fl. oz (500mL) to 33.8 fl.oz (1000mL) depending on size and condition.

- Keep away from children.